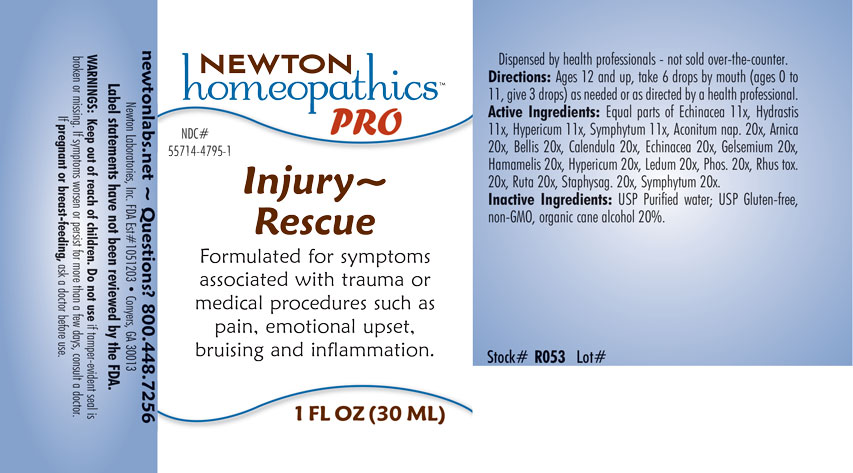 DRUG LABEL: Injury-Rescue
NDC: 55714-4795 | Form: LIQUID
Manufacturer: Newton Laboratories, Inc.
Category: homeopathic | Type: HUMAN OTC DRUG LABEL
Date: 20201204

ACTIVE INGREDIENTS: GOLDENSEAL 11 [hp_X]/1 mL; ACONITUM NAPELLUS 20 [hp_X]/1 mL; ARNICA MONTANA 20 [hp_X]/1 mL; BELLIS PERENNIS 20 [hp_X]/1 mL; CALENDULA OFFICINALIS FLOWERING TOP 20 [hp_X]/1 mL; ECHINACEA, UNSPECIFIED 20 [hp_X]/1 mL; GELSEMIUM SEMPERVIRENS ROOT 20 [hp_X]/1 mL; HAMAMELIS VIRGINIANA ROOT BARK/STEM BARK 20 [hp_X]/1 mL; HYPERICUM PERFORATUM 20 [hp_X]/1 mL; RHODODENDRON TOMENTOSUM LEAFY TWIG 20 [hp_X]/1 mL; PHOSPHORUS 20 [hp_X]/1 mL; TOXICODENDRON PUBESCENS LEAF 20 [hp_X]/1 mL; RUTA GRAVEOLENS FLOWERING TOP 20 [hp_X]/1 mL; DELPHINIUM STAPHISAGRIA SEED 20 [hp_X]/1 mL; COMFREY ROOT 20 [hp_X]/1 mL
INACTIVE INGREDIENTS: WATER; ALCOHOL

Injury 4795L

INACTIVE INGREDIENT SECTION

Inactive Ingredients: USP Purified Water; USP Gluten-free, non-GMO, organic cane alcohol 20%.

QUESTIONS

newtonlabs.net – Questions? 800.448.7256

Newton Laboratories, Inc. FDA Est # 1051203 - Conyers, GA 30013

DOSAGE & ADMINISTRATION SECTION

Directions: Ages 12 and up, take 6 drops by mouth (ages 0 to 11, give 3 drops) as needed or as directed by a health professional.

OTC - PURPOSE SECTION

Formulated for symptoms associated with trauma or medical procedures such as pain, emotional upset, bruising and inflammation.

WARNINGS SECTION

WARNINGS: Keep out of reach of children. Do not use if tamper-evident seal is broken or missing. If symptoms worsen or persist for more than a few days, consult a doctor. If pregnant or breast-feeding, ask a doctor before use.

OTC - PREGNANCY OR BREAST FEEDING SECTION

If pregnant or breast-feeding, ask a doctor before use.

OTC - KEEP OUT OF REACH OF CHILDREN SECTION

Keep out of reach of children.

OTC - ACTIVE INGREDIENT SECTION

Equal parts of Echinacea 6x, Hydrastis 6x, Hypericum 6x, Symphytum 6x, Aconitum nap. 15x, Arnica 15x, Bellis 15x, Calendula 15x, Echinacea 15x, Gelsemium 15x, Hamamelis 15x, Hypericum 15x, Ledum 15x, Phos. 15x, Rhus tox. 15x, Ruta 15x, Staphysag. 15x, Symphytum 15x,

INDICATIONS & USAGE SECTION

Formulated for symptoms associated with trauma or medical procedures such as pain, emotional upset, bruising and inflammation.